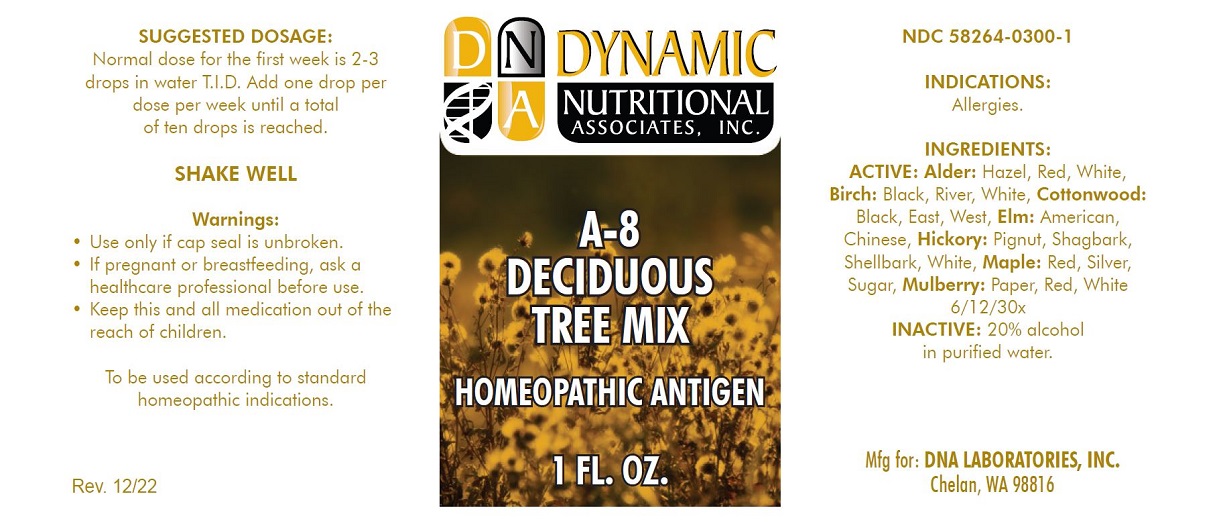 DRUG LABEL: A-8
NDC: 58264-0300 | Form: SOLUTION
Manufacturer: DNA Labs, Inc.
Category: homeopathic | Type: HUMAN OTC DRUG LABEL
Date: 20250109

ACTIVE INGREDIENTS: ALNUS RUBRA POLLEN 30 [hp_X]/1 mL; ALNUS SERRULATA POLLEN 30 [hp_X]/1 mL; ALNUS RHOMBIFOLIA POLLEN 30 [hp_X]/1 mL; BETULA LENTA POLLEN 30 [hp_X]/1 mL; BETULA NIGRA POLLEN 30 [hp_X]/1 mL; BETULA POPULIFOLIA POLLEN 30 [hp_X]/1 mL; ULMUS AMERICANA POLLEN 30 [hp_X]/1 mL; ULMUS PUMILA POLLEN 30 [hp_X]/1 mL; POPULUS BALSAMIFERA POLLEN 30 [hp_X]/1 mL; POPULUS DELTOIDES SUBSP. DELTOIDES POLLEN 30 [hp_X]/1 mL; POPULUS DELTOIDES SUBSP. MONILIFERA POLLEN 30 [hp_X]/1 mL; CARYA GLABRA POLLEN 30 [hp_X]/1 mL; CARYA OVATA POLLEN 30 [hp_X]/1 mL; CARYA LACINIOSA POLLEN 30 [hp_X]/1 mL; CARYA ALBA POLLEN 30 [hp_X]/1 mL; ACER RUBRUM POLLEN 30 [hp_X]/1 mL; ACER SACCHARUM POLLEN 30 [hp_X]/1 mL; ACER SACCHARINUM POLLEN 30 [hp_X]/1 mL; MORUS ALBA POLLEN 30 [hp_X]/1 mL; MORUS RUBRA POLLEN 30 [hp_X]/1 mL; BROUSSONETIA PAPYRIFERA POLLEN 30 [hp_X]/1 mL
INACTIVE INGREDIENTS: ALCOHOL; WATER

A-8

NDC 58264-0300-1

INDICATIONS

PURPOSE

Allergies.

INGREDIENTS

ACTIVE

Alder: Red, Tag, White 6/12/30x, Birch: Red, Black, White 6/12/30x, Elm: American, Chinese 6/12/30x, Cottonwood: East, West, Black 6/12/30x, Hickory: Pignut, Shagbark, Shellbark, White 6/12/30x, Maple: Red, Sugar, Silver 6/12/30x, Mulberry: White, Red, Paper 6/12/30x

INACTIVE

20% alcohol in purified water.

SUGGESTED DOSAGE

Normal dose for the first week is 2-3 drops in water T.I.D. Add one drop per dose per week until a total of ten drops is reached.

STORAGE AND HANDLING

SHAKE WELL

Warnings

- Use only if cap seal is unbroken.

PREGNANCY OR BREAST FEEDING

- If pregnant or breastfeeding, ask a healthcare professional before use.

KEEP OUT OF REACH OF CHILDREN

- Keep this and all medication out of the reach of children.

To be used according to standard homeopathic indications.

PRINCIPAL DISPLAY PANEL - 1 FL. OZ. Bottle Label

DYNAMIC
NUTRITIONAL
ASSOCIATES, INC.

A-8
DECIDUOUS
TREE MIX

HOMEOPATHIC ANTIGEN

1 FL. OZ.